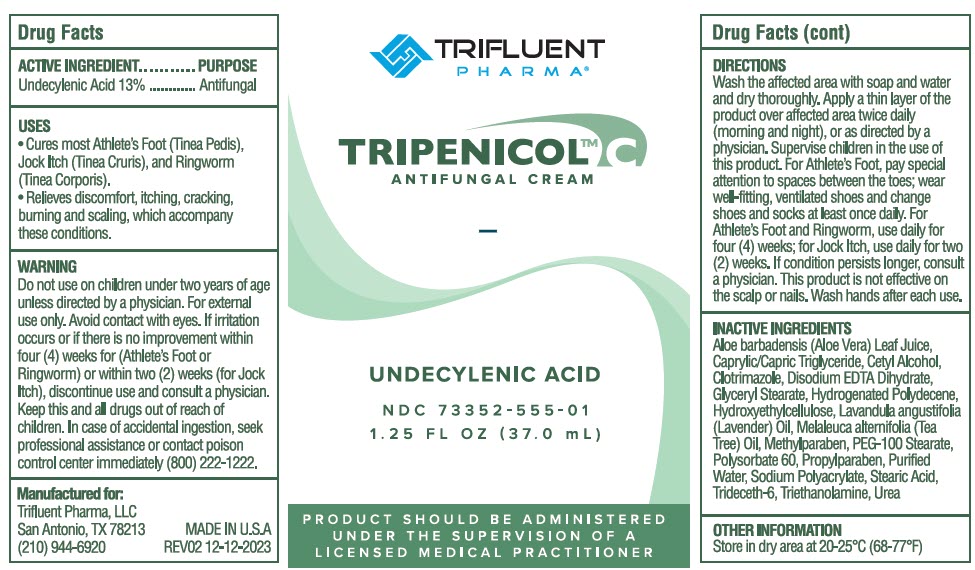 DRUG LABEL: Tripenicol C
NDC: 73352-555 | Form: CREAM
Manufacturer: Trifluent Pharma LLC
Category: otc | Type: HUMAN OTC DRUG LABEL
Date: 20251014

ACTIVE INGREDIENTS: UNDECYLENIC ACID 0.13 g/1 mL
INACTIVE INGREDIENTS: WATER; HYDROXYETHYL CELLULOSE, UNSPECIFIED; ALOE VERA LEAF; EDETATE DISODIUM; UREA; MEDIUM-CHAIN TRIGLYCERIDES; POLYSORBATE 60; PEG-100 MONOSTEARATE; CETYL ALCOHOL; GLYCERYL MONOSTEARATE; STEARIC ACID; METHYLPARABEN; PROPYLPARABEN; TROLAMINE; CLOTRIMAZOLE; LAVENDER OIL; TEA TREE OIL; SODIUM POLYACRYLATE (8000 MW); HYDROGENATED POLYDECENE (1500 CST); TRIDECETH-6

Tripenicol™ C

DRUG FACTS

ACTIVE INGREDIENT

Undecylenic Acid 13%

PURPOSE

Antifungal

USES

- Cures most Athlete's Foot (Tinea Pedis), Jock Itch (Tinea Cruris), and Ringworm (Tinea Corporis).
- Relives discomfort, itching, cracking, burning and scaling, which accompany these conditions.

WARNING

Do not use on children under two years of age unless directed by a physician. For external use only. Avoid contact with eyes. If irritation occurs or if there is no improvement within four (4) weeks (for Athlete's Foot or Ringworm) or within two (2) weeks (for Jock Itch), discontinue use and consult a physician.

KEEP OUT OF REACH OF CHILDREN

Keep this and all drugs out of reach of children. In case of accidental ingestion, seek professional assistance or contact poison control center immediately (800)-222-1222.

DIRECTIONS

Wash the affected area with soap and water and dry thoroughly. Apply a thin layer of the product over affected area twice daily (morning and night), or as directed by a physician. Supervise children in the use of this product. For Athlete's Foot, pay special attention to spaces between the toes; wear well-fitting, ventilated shoes and change shoes and socks at least once daily. For Athlete's Foot and Ringworm, use daily for four (4) weeks; for Jock Itch, use daily for two (2) weeks. If condition persists longer, consult a physician. This product is not effective on the scalp or nails. Wash hands after each use.

INACTIVE INGREDIENTS

Aloe barbadensis (Aloe Vera) Leaf Juice, Caprylic/Capric Triglyceride, Cetyl Alcohol, Clotrimazole, Disodium EDTA Dihydrate, Glyceryl Stearate, Hydrogenated Polydecene, Hydroxyethylcellulose, Lavandula angustifolia (Lavender) Oil, Melaleuca alternifolia (Tea Tree) Oil, Methylparaben, PEG-100 Stearate, Polysorbate 60, Propylparaben, Purified Water, Sodium Polyacrylate, Stearic Acid, Trideceth-6, Triethanolamine, Urea

OTHER INFORMATION

Store in dry area at 20-25°C (68-77°F)

PRINCIPAL DISPLAY PANEL - 37.0 mL Bottle Label

TRIFLUENT
PHARMA®

TRIPENICOL™ C
ANTIFUNGAL CREAM

UNDECYLENIC ACID

NDC 73352-555-01
1.25 FL OZ (37.0 mL)

PRODUCT SHOULD BE ADMINISTERED
UNDER THE SUPERVISION OF A
LICENSED MEDICAL PRACTITIONER